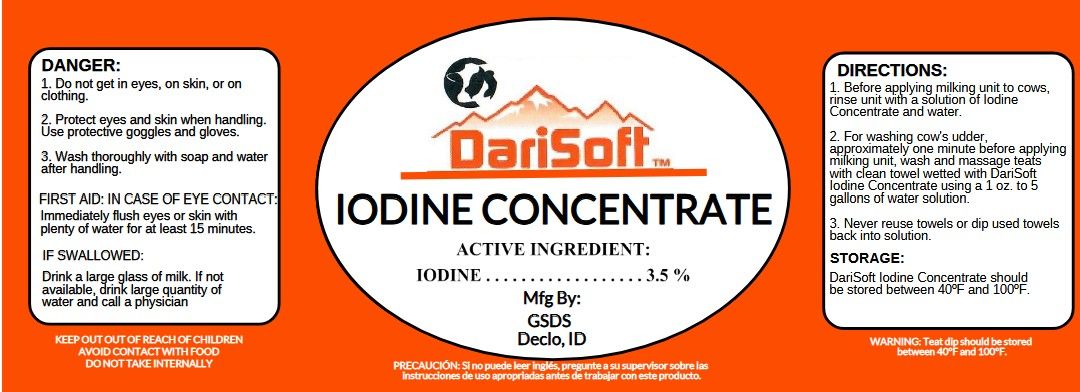 DRUG LABEL: DariSoft Iodine Concentrate
NDC: 86186-111 | Form: SOLUTION
Manufacturer: Gem State Dairy Supply
Category: animal | Type: OTC ANIMAL DRUG LABEL
Date: 20250719

ACTIVE INGREDIENTS: IODINE 3.5 g/1 L
INACTIVE INGREDIENTS: SURFACTIN

DariSoft™
Iodine Concentrate 3.5%

Active Ingredients:

Iodine............................3.5%

PURPOSE

Sanitizing Teat Dip

Directions:

1. Before applying milking unit to cows, rinse unit with a solution of iodine concentrate and water.

2. For washing cow's udder, approximately one minute before applying milking unit, wash and massage teats with clean towel wetted

with DariSoft iodine concentrate using a 1 oz. to 1 gallon of water solutions.

3. Never reuse towels or dip used towels back into solution.

PRECAUTIONS

Danager:

1. Do not get in eyes, on skin or on clothing.

2. Protect eyes and skin when handling. Use protective goggles and gloves.

3. Wash thoroughly with soap and water after handling.

FIRST AID:

IN CASE OF EYE CONTCT: Immediantly flush eyes or skin with plenty of water for at least 15 minutes.

IF SWALLOWED: Drink a large glass of milk. If not available, drink large quantity of water and call a physician.

WARNINGS

WARNING: DariSoft Iodine Concentrate should be stored between 40°F and 100°F.

KEEP OUT OF REACH OF CHILDREN

AVOID CONTACT WITH FOOD

DO NOT TAKE INTERNALLY